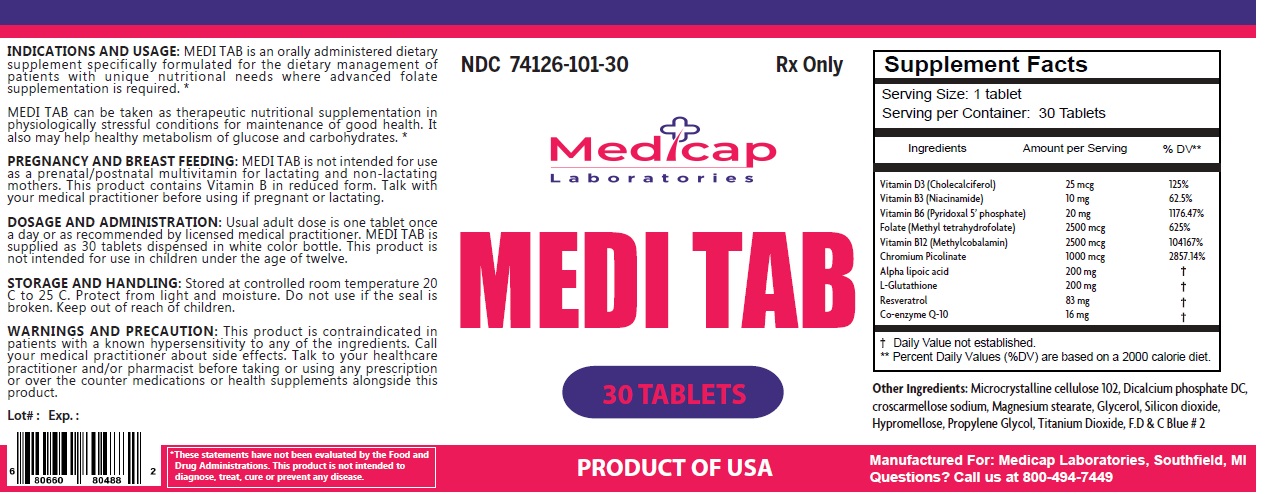 DRUG LABEL: MEDI TAB
NDC: 74126-101 | Form: TABLET
Manufacturer: Zurich Pharma Inc
Category: other | Type: DIETARY SUPPLEMENT
Date: 20240719

ACTIVE INGREDIENTS: CHOLECALCIFEROL 25 ug/1 1; NIACINAMIDE 10 mg/1 1; PYRIDOXAL PHOSPHATE ANHYDROUS 20 mg/1 1; 5-METHYLTETRAHYDROFOLIC ACID 2500 ug/1 1; METHYLCOBALAMIN 2500 ug/1 1; CHROMIUM PICOLINATE 1000 ug/1 1; ALPHA LIPOIC ACID 200 mg/1 1; GLUTATHIONE 200 mg/1 1; RESVERATROL 83 mg/1 1; UBIDECARENONE 16 mg/1 1
INACTIVE INGREDIENTS: MICROCRYSTALLINE CELLULOSE 102; DIBASIC CALCIUM PHOSPHATE DIHYDRATE; CROSCARMELLOSE SODIUM; MAGNESIUM STEARATE; GLYCERIN; SILICON DIOXIDE; HYPROMELLOSE, UNSPECIFIED; PROPYLENE GLYCOL; TITANIUM DIOXIDE; FD&C BLUE NO. 2

Medicap Laboratories MEDI TAB

STATEMENT OF IDENTITY

Supplement Facts
Serving Size: 1 tablet
Serving per Container: 30 Tablets
Ingredients | Amount per Serving | % DV**
Vitamin D3 (Cholecalciferol) | 25 mcg | 125%
Vitamin B3 (Niacinamide) | 10 mg | 62.5%
Vitamin B6 (Pyridoxal 5' phosphate) | 20 mg | 1176.47%
Folate (Methyl tetrahydrofolate) | 2500 mcg | 625%
Vitamin B12 (Methylcobalamin) | 2500 mcg | 104167%
Chromium Picolinate | 1000 mcg | 2857.14%
Alpha lipoic acid | 200 mg | †
L-Glutathione | 200 mg | †
Resveratrol | 83 mg | †
Coenzyme Q-10 | 16 mg | †
† Daily Value not established.
** Percent Daily Values (%DV) are based on a 2000 calorie diet.

Other Ingredients: Microcrystalline cellulose 102, Dicalcium phosphate DC, croscarmellose sodium, Magnesium stearate, Glycerol, Silicon dioxide, Hypromellose, Propylene Glycol, Titanium Dioxide, F.D & C Blue # 2

INDICATIONS AND USAGE:

MEDI TAB is an orally administered dietary supplement specifically formulated for the dietary management of patients with unique nutritional needs where advanced folate supplementation is required. *
MEDI TAB can be taken as therapeutic nutritional supplementation in physiologically stressful conditions for maintenance of good health. It also may help healthy metabolism of glucose and carbohydrates. *
PREGNANCY AND BREAST FEEDING:

MEDI TAB is not intended for use as a prenatal/postnatal multivitamin for lactating and non-lactating mothers. This product contains Vitamin B in reduced form. Talk with your medical practitioner before using if pregnant or lactating.

DOSAGE AND ADMINISTRATION:

Usual adult dose is one tablet once a day or as recommended by licensed medical practitioner. MEDI TAB is supplied as 30 tablets dispensed in white color bottle. This product is not intended for use in children under the age of twelve.

STORAGE AND HANDLING:

Stored at controlled room temperature 20 C to 25 C. Protect from light and moisture. Do not use if the seal is broken. Keep out of reach of children.

WARNINGS AND PRECAUTION:

This product is contraindicated in patients with a known hypersensitivity to any of the ingredients. Call your medical practitioner about side effects. Talk to your healthcare practitioner and/or pharmacist before taking or using any prescription or over the counter medications or health supplements alongside this product.

HEALTH CLAIM

Rx Only

PRODUCT OF USA

Manufactured For: Medicap Laboratories, Southfield, MI
Questions? Call us at 800-494-7449

*These statements have not been evaluated by the Food and Drug Administrations. This product is not intended to diagnose, treat, cure or prevent any disease.